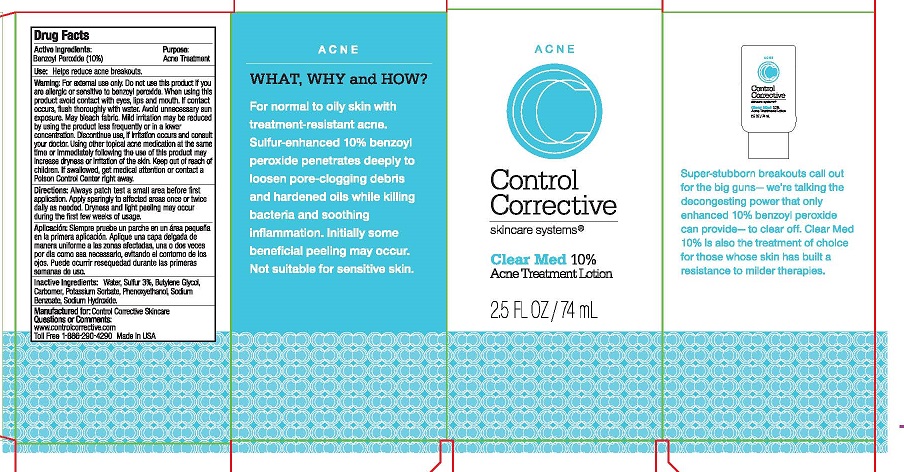 DRUG LABEL: CLEAR MED
NDC: 70764-107 | Form: LOTION
Manufacturer: CONTROL CORRECTIVE SKINCARE INC
Category: otc | Type: HUMAN OTC DRUG LABEL
Date: 20251231

ACTIVE INGREDIENTS: BENZOYL PEROXIDE 10 g/100 mL
INACTIVE INGREDIENTS: WATER; SULFUR; BUTYLENE GLYCOL; CARBOMER COPOLYMER TYPE A; POTASSIUM SORBATE; PHENOXYETHANOL; SODIUM BENZOATE; SODIUM HYDROXIDE

CONTROL CORRECTION - CLEAR MED 10% (70764-107)

ACTIVE INGREDIENTS

BENZOYL PEROXIDE 10%

PURPOSE

ACNE TREATMENT

USE

HELPS REDUCE ACNE BREAKOUTS.

WARNINGS

FOR EXTERNAL USE ONLY. DO NOT USE IF YOU ARE ALLERGIC OR SENSITIVE TO BENZOYL PEROXIDE. WHEN USING THIS PRODUCT AVOID CONTACT WITH EYES, LIPS AND MOUTH. IF CONTACT OCCURS, FLUSH THOROUGHLY WITH WATER. AVOID UNNECESSARY SUN EXPOSURE. MAY BLEACH FABRIC. MILD IRRITATION MAY BE REDUCED BY USING THE PRODUCT LESS FREQUENTLY OR IN A LOWER CONCENTRATION. DISCONTINUE USE, IF IRRITATION OCCURS AND CONSULT YOUR DOCTOR. USING OTHER TOPICAL ACNE MEDICATION AT THE SAME TIME OR IMMEDIATELY FOLLOWING USE OF THIS PRODUCT MAY INCREASE DRYNESS OR IRRITATION OF THE SKIN.

DIRECTIONS

ALWAYS PATCH TEST A SMALL AREA BEFORE FIRST APPLICATION. APPLY SPARINGLY TO AFFECTED AREAS ONCE OR TWICE DAILY AS NEEDED, AVOIDING THE EYE AREA. DRYNESS AND LIGHT PEELING MAY OCCUR DURING THE FIRST FEW WEEKS OF USAGE.

INACTIVE INGREDIENTS

WATER, SULFUR 3%, BUTYLENE GLYCOL, CARBOMER, POTASSIUM SORBATE, PHENOXYETHANOL, SODIUM BENZOATE, SODIUM HYDROXIDE.

KEEP OUT OF REACH OF CHILDREN. IF SWALLOWED, GET MEDICAL HELP OR CONTACT A POISON CONTROL CENTER RIGHT AWAY.

QUESTIONS OR COMMENTS:

WWW.CONTROLCORRECTIVE.COM

TOLL FREE 1-866-290-4290

MADE IN USA